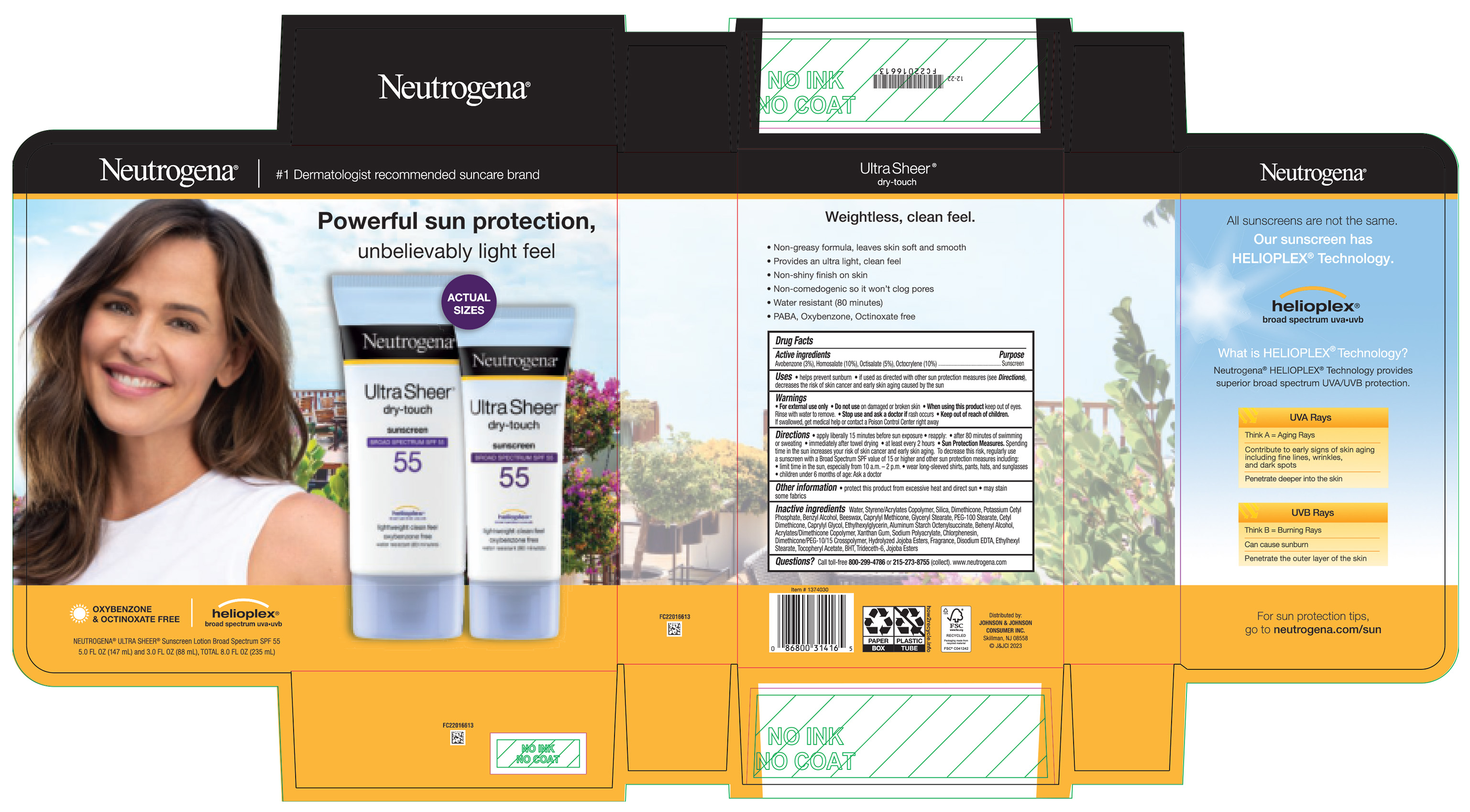 DRUG LABEL: Neutrogena Ultra Sheer Dry Touch Sunscreen Broad Spectrum SPF 55
NDC: 69968-0847 | Form: KIT | Route: TOPICAL
Manufacturer: Kenvue Brands LLC
Category: otc | Type: HUMAN OTC DRUG LABEL
Date: 20251106

ACTIVE INGREDIENTS: OCTOCRYLENE 100 mg/1 mL; HOMOSALATE 100 mg/1 mL; AVOBENZONE 30 mg/1 mL; OCTISALATE 50 mg/1 mL; OCTOCRYLENE 100 mg/1 mL; HOMOSALATE 100 mg/1 mL; OCTISALATE 50 mg/1 mL; AVOBENZONE 30 mg/1 mL
INACTIVE INGREDIENTS: ALPHA-TOCOPHEROL ACETATE; XANTHAN GUM; EDETATE DISODIUM ANHYDROUS; CAPRYLYL GLYCOL; JOJOBA OIL, RANDOMIZED; SILICON DIOXIDE; BENZYL ALCOHOL; ALUMINUM STARCH OCTENYLSUCCINATE; DIMETHICONE/PEG-10/15 CROSSPOLYMER; ETHYLHEXYL STEARATE; CETYL DIMETHICONE 25; PEG-100 STEARATE; TRIDECETH-6; 2-ETHYLHEXYL ACRYLATE, METHACRYLATE, METHYL METHACRYLATE, OR BUTYL METHACRYLATE/HYDROXYPROPYL DIMETHICONE COPOLYMER (30000-300000 MW); DOCOSANOL; DIMETHICONE; YELLOW WAX; HYDROLYZED JOJOBA ESTERS (ACID FORM); GLYCERYL MONOSTEARATE; ETHYLHEXYLGLYCERIN; CHLORPHENESIN; BUTYL METHACRYLATE/METHYL METHACRYLATE/METHACRYLIC ACID/STYRENE CROSSPOLYMER; BUTYLATED HYDROXYTOLUENE; WATER; POTASSIUM CETYL PHOSPHATE; CAPRYLYL TRISILOXANE; 2-ETHYLHEXYL ACRYLATE, METHACRYLATE, METHYL METHACRYLATE, OR BUTYL METHACRYLATE/HYDROXYPROPYL DIMETHICONE COPOLYMER (30000-300000 MW); XANTHAN GUM; EDETATE DISODIUM ANHYDROUS; CAPRYLYL GLYCOL; JOJOBA OIL, RANDOMIZED; SILICON DIOXIDE; BENZYL ALCOHOL; ALUMINUM STARCH OCTENYLSUCCINATE; DIMETHICONE/PEG-10/15 CROSSPOLYMER; ETHYLHEXYL STEARATE; CETYL DIMETHICONE 25; PEG-100 STEARATE; TRIDECETH-6; DOCOSANOL; DIMETHICONE; YELLOW WAX; HYDROLYZED JOJOBA ESTERS (ACID FORM); GLYCERYL MONOSTEARATE; ETHYLHEXYLGLYCERIN; CHLORPHENESIN; BUTYL METHACRYLATE/METHYL METHACRYLATE/METHACRYLIC ACID/STYRENE CROSSPOLYMER; BUTYLATED HYDROXYTOLUENE; WATER; POTASSIUM CETYL PHOSPHATE; CAPRYLYL TRISILOXANE; ALPHA-TOCOPHEROL ACETATE

Neutrogena Ultra Sheer Dry Touch Sunscreen Broad Spectrum SPF 55 - Club

Drug Facts

ACTIVE INGREDIENT

Active ingredients | Purpose
Avobenzone 3% | Sunscreen
Homosalate 10% | Sunscreen
Octisalate 5% | Sunscreen
Octocrylene 10% | Sunscreen

Uses

- helps prevent sunburn
- if used as directed with other sun protection measures (see Directions), decreases the risk of skin cancer and early skin aging caused by the sun

Warnings

For external use only

Do not use on damaged or broken skin

When using this product keep out of eyes. Rinse with water to remove.

Stop use and ask a doctor if rash occurs

Keep out of reach of children. If swallowed, get medical help or contact a Poison Control Center right away

Directions

- apply liberally 15 minutes before sun exposure
- reapply:
- after 80 minutes of swimming or sweating
- immediately after towel drying
- at least every 2 hours
- Sun Protection Measures. Spending time in the sun increases your risk of skin cancer and early skin aging. To decrease this risk, regularly use a sunscreen with a Broad Spectrum SPF value of 15 or higher and other sun protection measures including:
- limit time in the sun, especially from 10 a.m. - 2 p.m.
- wear long-sleeved shirts, pants, hats and sunglasses
- Children under 6 months of age: Ask a doctor

Other information

- protect this product from excessive heat and direct sun
- may stain some fabrics

Inactive ingredients

Water, Styrene/Acrylates Copolymer, Silica, Dimethicone, Potassium Cetyl Phosphate, Benzyl Alcohol, Beeswax, Caprylyl Methicone, Glyceryl Stearate, PEG-100 Stearate, Cetyl Dimethicone, Caprylyl Glycol, Ethylhexylglycerin, Aluminum Starch Octenylsuccinate, Behenyl Alcohol, Acrylates/Dimethicone Copolymer, Xanthan Gum, Sodium Polyacrylate, Chlorphenesin, Dimethicone PEG - 10/15 Crosspolymer, Hydrolyzed Jojoba Esters, Fragrance, Disodium EDTA, Ethylhexyl Stearate, Tocopheryl Acetate, BHT, Trideceth-6, Jojoba Esters

Questions?

Call toll-free 800-299-4786 or 215-273-8755 (collect). www.neutrogena.com

Distributed by:
JOHNSON & JOHNSON CONSUMER INC.
Skillman, NJ 08558

PRINCIPAL DISPLAY PANEL - Kit Package Label

Neutrogena®

#1 Dermatologist recommended suncare brand

Powerful sun protection,

unbelievably light feel

ACTUAL

SIZES

OXYBENZONE

& OCTINOXATE FREE

helioplex®

broad spectrum uva•uvb

NEUTROGENA® ULTRA SHEER® Sunscreen Lotion Broad Spectrum SPF 55

5.0 FL OZ (147 mL) and 3.0 FL OZ (88 mL), TOTAL 8.0 FL OZ (235 mL)